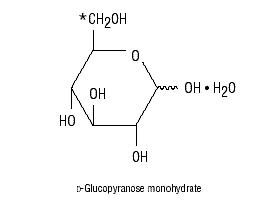 DRUG LABEL: Unknown
Manufacturer: Baxter Healthcare Corporation
Category: prescription | Type: HUMAN PRESCRIPTION DRUG LABELING
Date: 20060413

Plasma-Lyte® 148 and 5% Dextrose Injection
(Multiple Electrolytes and Dextrose Injection, Type 1, USP)
in Viaflex® Plastic Container

DESCRIPTION

Plasma-Lyte® 148 and 5% Dextrose Injection (Multiple Electrolytes and Dextrose Injection, Type 1, USP) is a sterile, nonpyrogenic solution for fluid and electrolyte replenishment and caloric supply in a single dose container for intravenous administration. Each 100 mL contains 5 g Dextrose Hydrous, USP*, 526 mg Sodium Chloride, USP (NaCl); 502 mg Sodium Gluconate (C6H11NaO7); 368 mg Sodium Acetate Trihydrate, USP (C2H3NaO2•3H2O), 37 mg Potassium Chloride, USP (KCl); and 30 mg Magnesium Chloride, USP (MgCl2•6H2O). It contains no antimicrobial agents. The pH is 5.0 (4.0 to 6.5). The pH is adjusted with hydrochloric acid.

Plasma-Lyte® 148 and 5% Dextrose Injection (Multiple Electrolytes and Dextrose Injection, Type 1, USP) administered intravenously has value as a source of water, electrolytes, and calories. One liter has an ionic concentration of 140 mEq sodium, 5 mEq potassium, 3 mEq magnesium, 98 mEq chloride, 27 mEq acetate and 23 mEq gluconate. The osmolarity is 547 mOsmol/L (calc). Normal physiologic osmolarity range is approximately 280 to 310 mOsmol/L. Administration of substantially hypertonic solutions (≥ 600 mOsmol/L) may cause vein damage. The caloric content is 190 kcal/L.

The Viaflex® plastic container is fabricated from a specially formulated polyvinyl chloride (PL 146® Plastic). The amount of water that can permeate from inside the container into the overwrap is insufficient to affect the solution significantly. Solutions in contact with the plastic container may leach out certain chemical components from the plastic in very small amounts; however, biological testing was supportive of the safety of the plastic container materials.

CLINICAL PHARMACOLOGY

Plasma-Lyte® 148 and 5% Dextrose Injection (Multiple Electrolytes and Dextrose Injection, Type 1, USP) has value as a source of water, electrolytes, and calories. It is capable of inducing diuresis depending on the clinical condition of the patient.

Plasma-Lyte® 148 and 5% Dextrose Injection (Multiple Electrolytes and Dextrose Injection, Type 1, USP) produces a metabolic alkalinizing effect. Acetate and gluconate ions are metabolized ultimately to carbon dioxide and water, which requires the consumption of hydrogen cations.

INDICATIONS AND USAGE

Plasma-Lyte® 148 and 5% Dextrose Injection (Multiple Electrolytes and Dextrose Injection, Type 1, USP) is indicated as a source of water, electrolytes, and calories, or as an alkalinizing agent.

CONTRAINDICATIONS

Solutions containing dextrose may be contraindicated in patients with known allergy to corn or corn products.

WARNINGS

Plasma-Lyte® 148 and 5% Dextrose Injection (Multiple Electrolytes and Dextrose Injection, Type 1, USP) should be used with great care, if at all, in patients with congestive heart failure, severe renal insufficiency and in clinical states in which there exists edema with sodium retention.

Plasma-Lyte® 148 and 5% Dextrose Injection (Multiple Electrolytes and Dextrose Injection, Type 1, USP) should be used with great care, if at all, in patients with hyperkalemia, severe renal failure and in conditions in which potassium retention is present.

Plasma-Lyte® 148 and 5% Dextrose Injection (Multiple Electrolytes and Dextrose Injection, Type 1, USP) should be used with great care in patients with metabolic or respiratory alkalosis. The administration of acetate or gluconate ions should be done with great care in those conditions in which there is an increased level or an impaired utilization of these ions, such as severe hepatic insufficiency.

The intravenous administration of Plasma-Lyte® 148 and 5% Dextrose Injection (Multiple Electrolytes and Dextrose Injection, Type 1, USP) can cause fluid and/or solute overloading resulting in dilution of serum electrolyte concentrations, overhydration, congested states, or pulmonary edema. The risk of dilutional states is inversely proportional to the electrolyte concentrations of the injection. The risk of solute overload causing congested states with peripheral and pulmonary edema is directly proportional to the electrolyte concentrations of the injection.

In patients with diminished renal function, administration of Plasma-Lyte® 148 and 5% Dextrose Injection (Multiple Electrolytes and Dextrose Injection, Type 1, USP) may result in sodium or potassium retention.

GENERAL PRECAUTIONS

Clinical evaluation and periodic laboratory determinations are necessary to monitor changes in fluid balance, electrolyte concentrations and acid base balance during prolonged parenteral therapy or whenever the condition of the patient warrants such evaluation.

Plasma-Lyte® 148 and 5% Dextrose Injection (Multiple Electrolytes and Dextrose Injection, Type 1, USP) should be used with caution. Excess administration may result in metabolic alkalosis.

Caution must be exercised in the administration of Plasma-Lyte® 148 and 5% Dextrose Injection (Multiple Electrolytes and Dextrose Injection, Type 1, USP) to patients receiving corticosteroids or corticotropin.

Plasma-Lyte® 148 and 5% Dextrose Injection (Multiple Electrolytes and Dextrose Injection, Type 1, USP) should be used with caution in patients with overt or subclinical diabetes mellitus.

Pregnancy

Teratogenic Effects

Pregnancy Category C

Animal reproduction studies have not been conducted with Plasma-Lyte® 148 and 5% Dextrose Injection (Multiple Electrolytes and Dextrose Injection, Type 1, USP). It is also not known whether Plasma-Lyte® 148 and 5% Dextrose Injection (Multiple Electrolytes and Dextrose Injection, Type 1, USP) can cause fetal harm when administered to a pregnant woman or can affect reproduction capacity. Plasma-Lyte® 148 and 5% Dextrose Injection (Multiple Electrolytes and Dextrose Injection, Type 1, USP) should be given to a pregnant woman only if clearly needed.

Pediatric Use

Safety and effectiveness of Plasma-Lyte® 148 and 5% Dextrose Injection (Multiple Electrolytes and Dextrose Injection, Type 1, USP) in pediatric patients have not been established by adequate and well controlled trials, however, the use of plasmalyte and dextrose solutions in the pediatric population is referenced in the medical literature. The warnings, precautions and adverse reactions identified in the label copy should be observed in the pediatric population.

In very low birth weight infants, excessive or rapid administration of dextrose injection may result in increased serum osmolality and possible hemorrhage.

Carcinogenesis and Mutagenesis and Impairment of Fertility

Studies with Plasma-Lyte® 148 and 5% Dextrose Injection (Multiple Electrolytes and Dextrose Injection, Type 1, USP) have not been performed to evaluate carcinogenic potential, mutagenic potential, or effects on fertility.

Nursing Mothers

It is not known whether this drug is excreted in human milk. Because many drugs are excreted in human milk, caution should be exercised when Plasma-Lyte® 148 and 5% Dextrose Injection (Multiple Electrolytes and Dextrose Injection, Type 1, USP) is administered to a nursing mother.

Geriatric Use

Clinical studies of Plasma-Lyte® 148 and 5% Dextrose Injection (Multiple Electrolytes and Dextrose Injection, Type 1, USP) did not include sufficient numbers of subjects aged 65 and over to determine whether they respond differently from younger subjects. Other reported clinical experience has not identified differences in responses between the elderly and younger patients. In general, dose selection for an elderly patient should be cautious, usually starting at the low end of the dosing range, reflecting the greater frequency of decreased hepatic, renal, or cardiac function, and of concomitant disease or drug therapy.

Do not administer unless solution is clear and seal is intact.

ADVERSE REACTIONS

Reactions which may occur because of the solution or the technique of administration include febrile response, infection at the site of injection, venous thrombosis or phlebitis extending from the site of injection, extravasation and hypervolemia.

If an adverse reaction does occur, discontinue the infusion, evaluate the patient, institute appropriate therapeutic countermeasures, and save the remainder of the fluid for examination if deemed necessary.

DOSAGE AND ADMINISTRATION

As directed by a physician. Dosage is dependent upon the age, weight and clinical condition of the patient as well as laboratory determinations.

Parenteral drug products should be inspected visually for particulate matter and discoloration prior to administration whenever solution and container permit.

All injections in Viaflex® plastic containers are intended for intravenous administration using sterile equipment.

As reported in the literature, the dosage and constant infusion rate of intravenous dextrose must be selected with caution in pediatric patients, particularly neonates and low weight infants, because of the increased risk of hyperglycemia/hypoglycemia.

Additives may be incompatible. Complete information is not available. Those additives known to be incompatible should not be used. Consult with pharmacist, if available. If, in the informed judgment of the physician, it is deemed advisable to introduce additives, use aseptic technique. Mix thoroughly when additives have been introduced. Do not store solutions containing additives.

HOW SUPPLIED

Plasma-Lyte® 148 and 5% Dextrose Injection (Multiple Electrolytes and Dextrose Injection, Type 1, USP) in Viaflex® plastic containers is available as shown below:

Size (mL) | Code | NDC
1000 | 2B2584 | NDC 0338-0149-04
500 | 2B2583 | NDC 0338-0149-03

Exposure of pharmaceutical products to heat should be minimized. Avoid excessive heat. It is recommended the product be stored at room temperature (25°C); brief exposure up to 40°C does not adversely affect the product.

DIRECTIONS FOR USE OF VIAFLEX® PLASTIC CONTAINER

Warning: Do not use plastic containers in series connections. Such use could result in air embolism due to residual air being drawn from the primary container before administration of the fluid from the secondary container is completed.

To Open

Tear overwrap down side at slit and remove solution container. Some opacity of the plastic due to moisture absorption during the sterilization process may be observed. This is normal and does not affect the solution quality or safety. The opacity will diminish gradually. Check for minute leaks by squeezing inner bag firmly. If leaks are found, discard solution as sterility may be impaired. If supplemental medication is desired, follow directions below.

Preparation for Administration

1. Suspend container from eyelet support.

2. Remove plastic protector from outlet port at bottom of container.

3. Attach administration set. Refer to complete directions accompanying set.

Warning:

Additives may be incompatible.

To add medication before solution administration

1. Prepare medication site.

2. Using syringe with 19 to 22 gauge needle, puncture resealable medication port and inject.

3. Mix solution and medication thoroughly. For high density medication such as potassium chloride, squeeze ports while ports are upright and mix thoroughly.

To add medication during solution administration

1. Close clamp on the set.

2. Prepare medication site.

3. Using syringe with 19 to 22 gauge needle, puncture resealable medication port and inject.

4. Remove container from IV pole and/or turn to an upright position.

5. Evacuate both ports by squeezing them while container is in the upright position.

6. Mix solution and medication thoroughly.

7. Return container to in use position and continue administration.

Baxter Healthcare Corporation

Deerfield, IL 60015 USA

Printed in USA

©Copyright 1982, 1983, 1989, 1993, Baxter Healthcare Corporation.

All rights reserved.

7-19-22-968